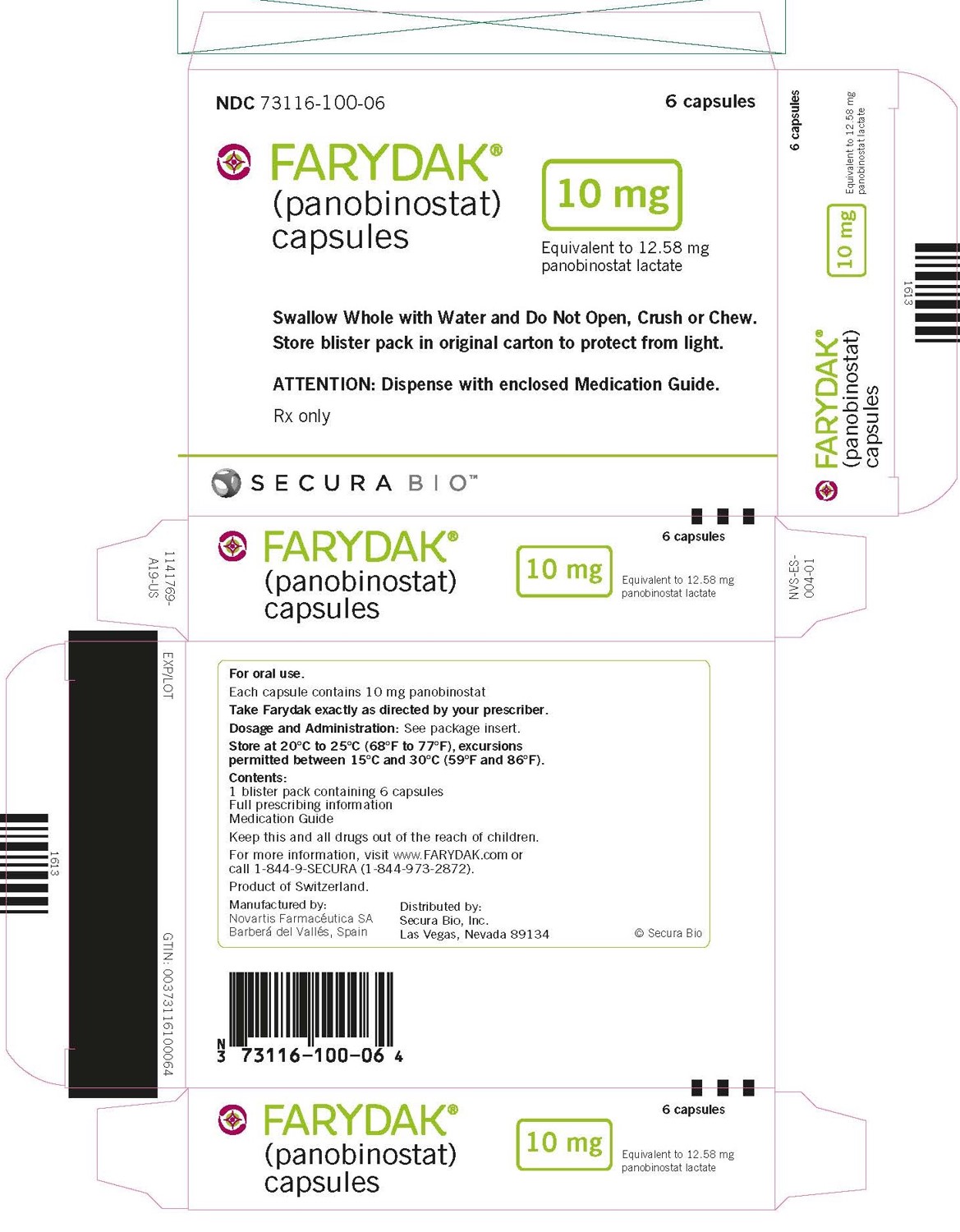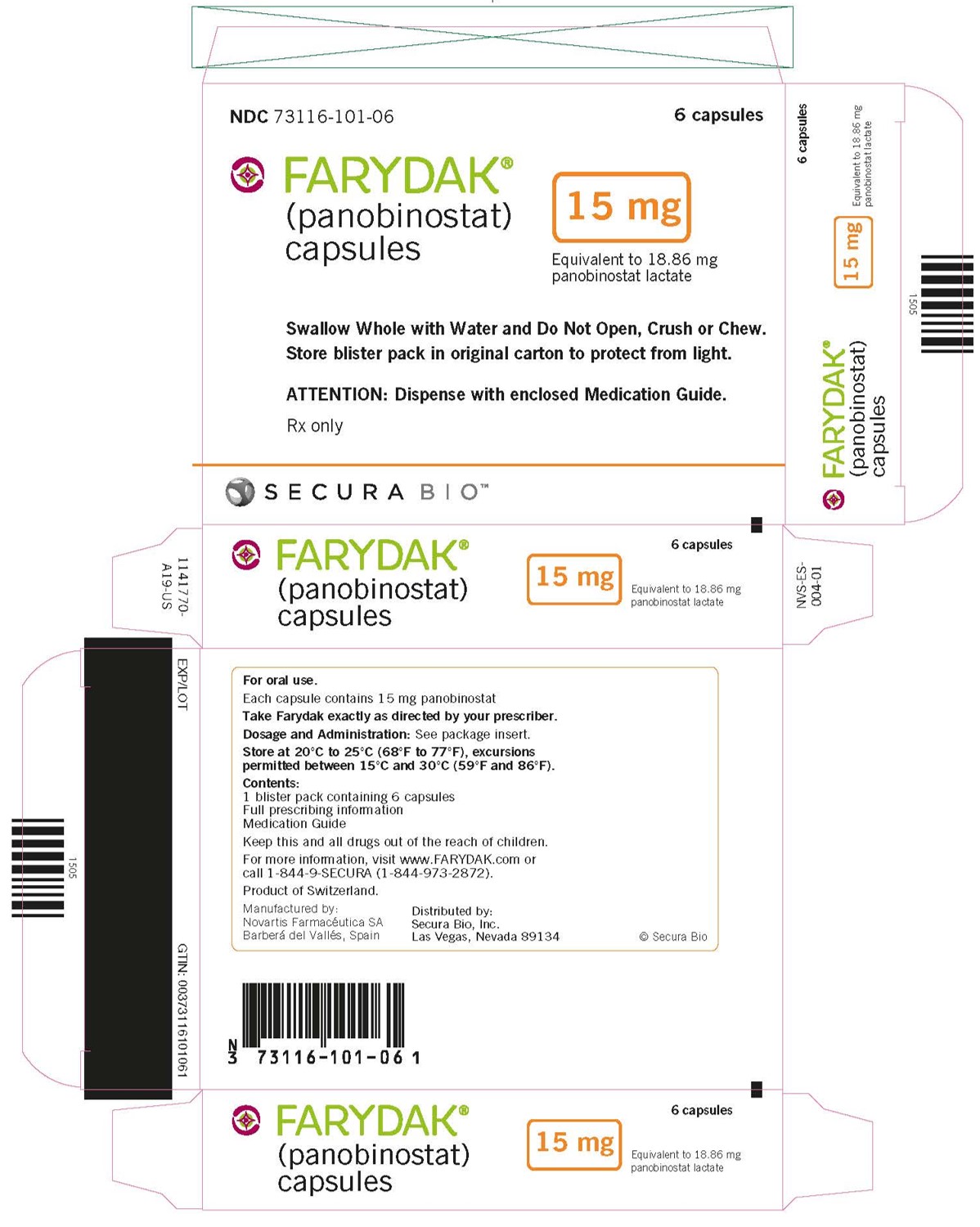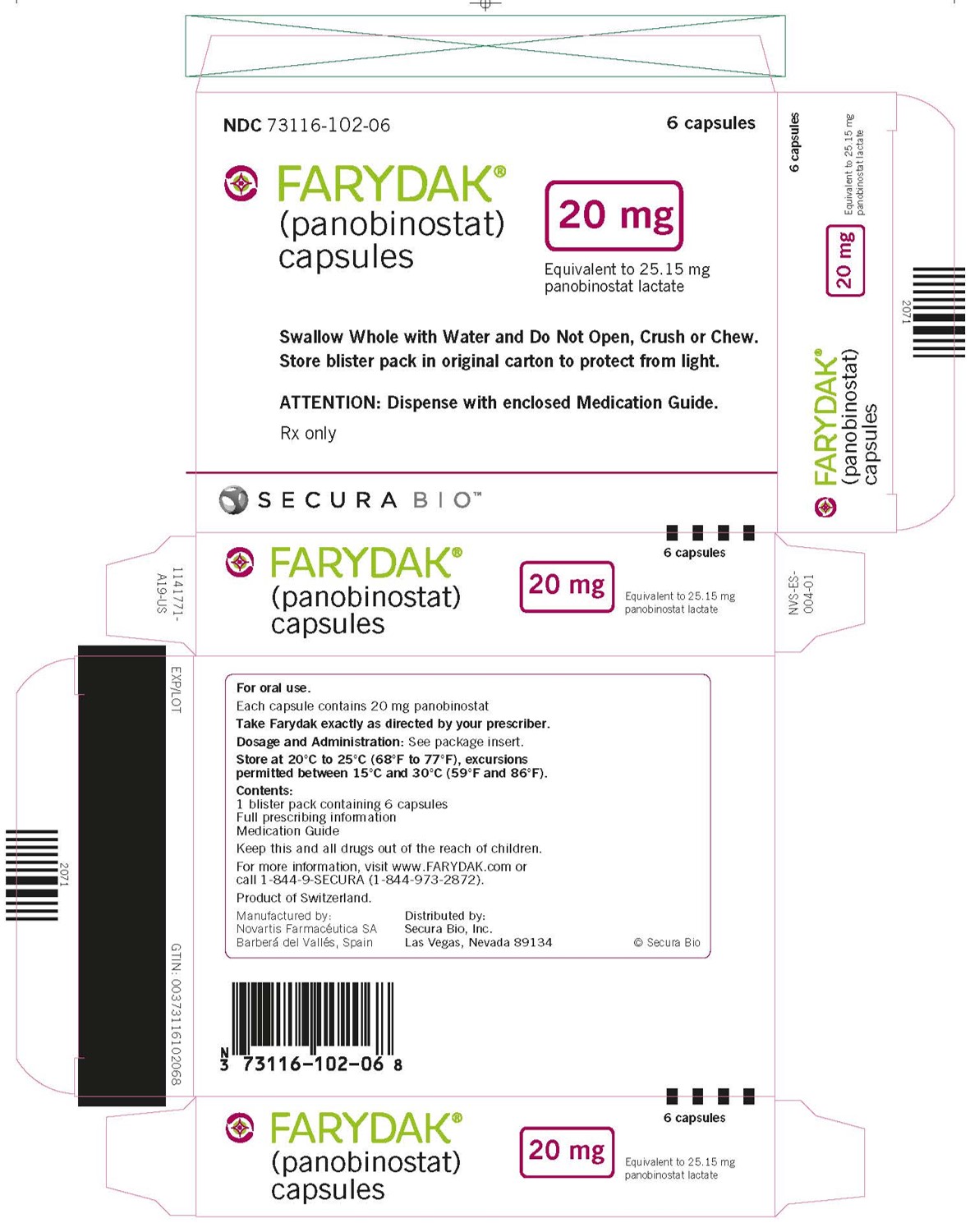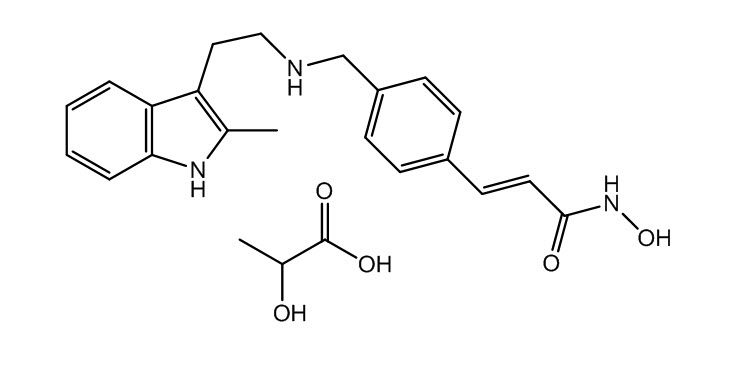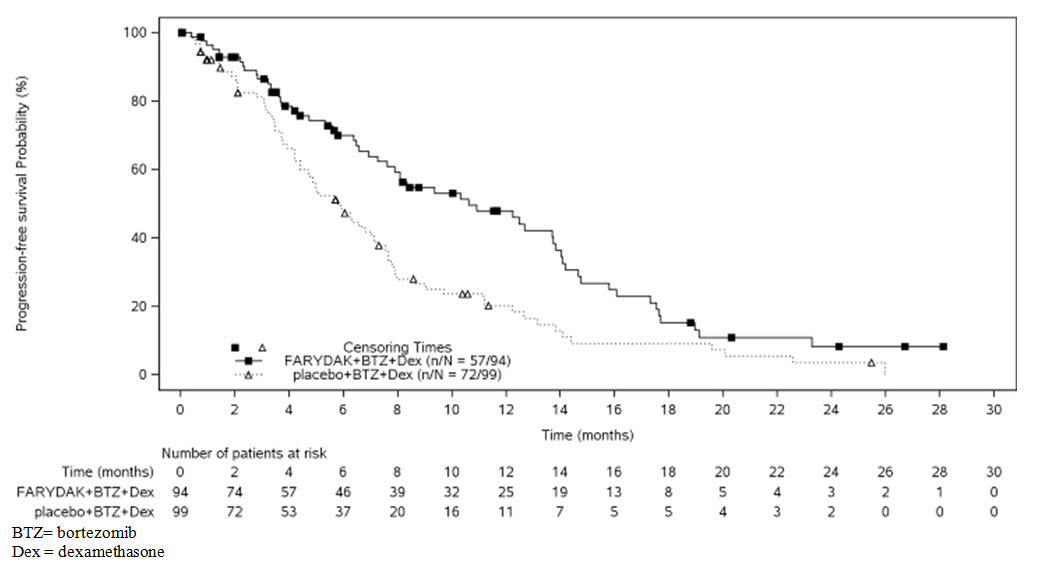 DRUG LABEL: FARYDAK
NDC: 73116-100 | Form: CAPSULE
Manufacturer: Secura Bio, Inc.
Category: prescription | Type: HUMAN PRESCRIPTION DRUG LABEL
Date: 20210727

ACTIVE INGREDIENTS: PANOBINOSTAT LACTATE 10 mg/1 1
INACTIVE INGREDIENTS: MAGNESIUM STEARATE; MANNITOL; CELLULOSE, MICROCRYSTALLINE; STARCH, CORN; GELATIN; FD&C BLUE NO. 1; FERRIC OXIDE YELLOW; TITANIUM DIOXIDE

HIGHLIGHTS OF PRESCRIBING INFORMATION

These highlights do not include all the information needed to use FARYDAK safely and effectively. See full prescribing information for FARYDAK.
FARYDAK® (panobinostat) capsules, for oral use
Initial U.S. Approval: 2015

RECENT MAJOR CHANGES

Warnings and Precautions, Embryo-Fetal Toxicity (5.7) | 6/2016

WARNING: FATAL AND SERIOUS TOXICITIES: SEVERE DIARRHEA AND CARDIAC TOXICITIES

See full prescribing information for complete boxed warning.

- Severe diarrhea occurred in 25% of FARYDAK treated patients. Monitor for symptoms, institute anti-diarrheal treatment, interrupt FARYDAK and then reduce dose or discontinue FARYDAK. (5.1)
- Severe and fatal cardiac ischemic events, severe arrhythmias, and ECG changes have occurred in patients receiving FARYDAK. Arrhythmias may be exacerbated by electrolyte abnormalities. Obtain ECG and electrolytes at baseline and periodically during treatment as clinically indicated. (5.2)

1 INDICATIONS AND USAGE

FARYDAK, a histone deacetylase inhibitor, in combination with bortezomib and dexamethasone, is indicated for the treatment of patients with multiple myeloma who have received at least 2 prior regimens, including bortezomib and an immunomodulatory agent. This indication is approved under accelerated approval based on progression free survival. Continued approval for this indication may be contingent upon verification and description of clinical benefit in confirmatory trials. (1)

2 DOSAGE AND ADMINISTRATION

- 20 mg, taken orally once every other day for 3 doses per week (on Days 1, 3, 5, 8, 10, and 12) of Weeks 1 and 2 of each 21-day cycle for 8 cycles (2.1)
- Consider continuing treatment for an additional 8 cycles for patients with clinical benefit, unless they have unresolved severe or medically significant toxicity (2.1)

3 DOSAGE FORMS AND STRENGTHS

Capsules: 10 mg, 15 mg, and 20 mg panobinostat (equivalent to 12.58 mg, 18.86 mg, and 25.15 mg respectively of panobinostat lactate) (3)

4 CONTRAINDICATIONS

None (4)

5 WARNINGS AND PRECAUTIONS

- Hemorrhage: Fatal and serious cases of gastrointestinal and pulmonary hemorrhage. Monitor platelet counts and transfuse as needed. (5.3)
- Hepatotoxicity: Monitor hepatic enzymes and adjust dosage if abnormal liver function tests are observed during FARYDAK therapy. (5.6)
- Embryo-Fetal Toxicity: can cause fetal harm. Advise women of the potential hazard to the fetus and to avoid pregnancy while taking FARYDAK. (5.7)

6 ADVERSE REACTIONS

The most common adverse reactions (incidence of at least 20%) in clinical studies are diarrhea, fatigue, nausea, peripheral edema, decreased appetite, pyrexia, and vomiting. (6.1)

The most common non-hematologic laboratory abnormalities (incidence ≥40%) are hypophosphatemia, hypokalemia, hyponatremia, and increased creatinine. The most common hematologic laboratory abnormalities (incidence ≥60%) are thrombocytopenia, lymphopenia, leukopenia, neutropenia, and anemia. (6.1)

To report SUSPECTED ADVERSE REACTIONS, contact Secura Bio, Inc. at 1-844-973-2872 or FDA at 1-800-FDA-1088 or www.fda.gov/medwatch.

7 DRUG INTERACTIONS

- Strong CYP3A4 inhibitors: Reduce FARYDAK dose. (7.1)
- Strong CYP3A4 inducers: Avoid concomitant use with FARYDAK. (7.2)
- Sensitive CYP2D6 substrates: Avoid concomitant use with FARYDAK. (7.3)
- Anti-arrhythmic drugs/QT-prolonging drugs: Avoid concomitant use. (7.4)

8 USE IN SPECIFIC POPULATIONS

Hepatic Impairment: Hepatic impairment can increase panobinostat exposure. Reduce FARYDAK dose in patients with mild or moderate hepatic impairment. Avoid use in patients with severe hepatic impairment. (8.6)

FULL PRESCRIBING INFORMATION

WARNING: FATAL AND SERIOUS TOXICITIES: SEVERE DIARRHEA AND CARDIAC TOXICITIES

Severe diarrhea occurred in 25% of FARYDAK treated patients. Monitor for symptoms, institute anti-diarrheal treatment, interrupt FARYDAK and then reduce dose or discontinue FARYDAK. (5.1)

Severe and fatal cardiac ischemic events, severe arrhythmias, and ECG changes have occurred in patients receiving FARYDAK. Arrhythmias may be exacerbated by electrolyte abnormalities. Obtain ECG and electrolytes at baseline and periodically during treatment as clinically indicated. (5.2)

1 INDICATIONS AND USAGE

FARYDAK, a histone deacetylase inhibitor, in combination with bortezomib and dexamethasone, is indicated for the treatment of patients with multiple myeloma who have received at least 2 prior regimens, including bortezomib and an immunomodulatory agent. This indication is approved under accelerated approval based on progression free survival [see Clinical Studies (14.1)]. Continued approval for this indication may be contingent upon verification and description of clinical benefit in confirmatory trials.

2 DOSAGE AND ADMINISTRATION

2.1 Recommended Dosing

The recommended starting dose of FARYDAK is 20 mg, taken orally once every other day for 3 doses per week in Weeks 1 and 2 of each 21-day cycle for up to 8 cycles. Consider continuing treatment for an additional 8 cycles for patients with clinical benefit who do not experience unresolved severe or medically significant toxicity. The total duration of treatment may be up to 16 cycles (48 weeks). FARYDAK is administered in combination with bortezomib and dexamethasone as shown in Table 1 and Table 2.

The recommended dose of bortezomib is 1.3 mg/m^2 given as an injection. The recommended dose of dexamethasone is 20 mg taken orally per scheduled day, on a full stomach.

Table 1: Recommended Dosing Schedule of FARYDAK in Combination with Bortezomib and Dexamethasone During Cycles 1 to 8
21-Day Cycle
Cycles 1 to 8 (3-Week cycles) | Week 1 Days |  |  |  |  |  |  | Week 2 Days |  |  |  |  |  |  | Week 3
FARYDAK | 1 |  | 3 |  | 5 |  |  | 8 |  | 10 |  | 12 |  |  | Rest period
Bortezomib | 1 |  |  | 4 |  |  |  | 8 |  |  | 11 |  |  |  | Rest period
Dexamethasone | 1 | 2 |  | 4 | 5 |  |  | 8 | 9 |  | 11 | 12 |  |  | Rest period

Table 2: Recommended Dosing Schedule of FARYDAK in Combination with Bortezomib and Dexamethasone During Cycles 9 to 16
21-Day Cycle
Cycles 9 to 16 (3-Week cycles) | Week 1 Days |  |  |  |  |  |  | Week 2 Days |  |  |  |  |  |  | Week 3
FARYDAK | 1 |  | 3 |  | 5 |  |  | 8 |  | 10 |  | 12 |  |  | Rest period
Bortezomib | 1 |  |  |  |  |  |  | 8 |  |  |  |  |  |  | Rest period
Dexamethasone | 1 | 2 |  |  |  |  |  | 8 | 9 |  |  |  |  |  | Rest period

2.2 Administration and Monitoring Instructions

FARYDAK should be taken orally once on each scheduled day at about the same time, either with or without food [see Clinical Pharmacology (12.3)].

FARYDAK capsules should be swallowed whole with a cup of water. Do not open, crush, or chew the capsules [see How Supplied/Storage and Handling (16)].

If a dose is missed it can be taken up to 12 hours after the specified dose time. If vomiting occurs the patient should not repeat the dose, but should take the next usual scheduled dose.

Counsel patients on the correct dosing schedule, technique of administration of FARYDAK, and when to take FARYDAK if dosing adjustments are made.

Prior to the start of FARYDAK treatment and during treatment, monitoring should include:

- Complete Blood Count (CBC): Obtain a CBC before initiating treatment. Verify that the baseline platelet count is at least 100 x 10^9/L and the baseline absolute neutrophil count (ANC) is at least 1.5 x 10^9/L. Monitor the CBC weekly (or more often as clinically indicated) during treatment. [see Warnings and Precautions (5.4) Adverse Reactions (6.1)].
- ECG: Perform an ECG prior to the start of therapy and repeat periodically during treatment as clinically indicated. Verify that the QTcF is less than 450 msec prior to initiation of treatment with FARYDAK. If during treatment with FARYDAK, the QTcF increases to ≥480 msec, interrupt treatment. Correct any electrolyte abnormalities. If QT prolongation does not resolve, permanently discontinue treatment with FARYDAK [see Warnings and Precautions (5.2), Adverse Reactions (6.1)]. During the clinical trial, ECGs were performed at baseline and prior to initiation of each cycle for the first 8 cycles.
- Serum Electrolytes: Obtain electrolytes, including potassium and magnesium, at baseline and monitor during therapy. Correct abnormal electrolyte values before treatment [see Warnings and Precautions (5.2), Adverse Reactions (6.1)]. During the trial, monitoring was conducted prior to the start of each cycle, at Day 11 of cycles 1 to 8, and at the start of each cycle for cycles 9 to 16.

For additional information please refer to the bortezomib and dexamethasone prescribing information.

2.3 Dose Adjustments and Modifications for Toxicity

Dose and/or schedule modification of FARYDAK may be required based on toxicity. Management of adverse drug reactions may require treatment interruption and/or dose reductions. If dose reduction is required, the dose of FARYDAK should be reduced in increments of 5 mg (i.e., from 20 mg to 15 mg, or from 15 mg to 10 mg). If the dosing of FARYDAK is reduced below 10 mg given 3 times per week, discontinue FARYDAK. Keep the same treatment schedule (3-week treatment cycle) when reducing dose. The table also lists Bortezomib (BTZ) dose modification procedures from the clinical trials.

Table 3: Dose Modifications for Most Common Toxicities
Thrombocytopenia | Platelets <50 x 10^9/L CTCAE Grade 3 |  | Platelets <50 x 10^9/L with bleeding CTCAE Grade 3 | Platelets <25 x 10^9/L CTCAE Grade 4
 | Maintain FARYDAK dose. Monitor platelet counts at least weekly. |  | Interrupt FARYDAK. Monitor platelet counts at least weekly until ≥50 x 10^9/L, then restart at reduced dose | Interrupt FARYDAK. Monitor platelet counts at least weekly until ≥50 x 10^9/L, then restart at reduced dose
 | Maintain BTZ dose |  | - Interrupt BTZ until thrombocytopenia resolves to ≥ 50 x 10^9/L - If only 1 dose was omitted prior to correction to these levels, restart BTZ at same dose - If 2 or more doses were omitted consecutively, or within the same cycle, BTZ should be restarted at a reduced dose
Neutropenia | ANC 0.75 to 1.0 x 10^9/L CTCAE Grade 3 | ANC 0.5 to 0.75 x 10^9/L CTCAE Grade 3 (2 or more occurrences) | ANC <1.0 x 10^9/L (CTCAE Grade 3) with febrile Neutropenia (any grade) | ANC <0.5 x 10^9/L CTCAE Grade 4
 | Maintain FARYDAK dose. | Interrupt FARYDAK until ANC ≥1.0 x 10^9/L, then restart at same dose | Interrupt FARYDAK until febrile neutropenia resolves and ANC ≥1.0 x 10^9/L, then restart at reduced dose | Interrupt FARYDAK until ANC ≥1.0 x 10^9/L, then restart at reduced dose
 | Maintain BTZ dose |  | - Interrupt BTZ until febrile neutropenia resolves and ANC ≥1.0 x 10^9/L - If only 1 dose was omitted prior to correction to these levels, restart BTZ at same dose - If 2 or more doses were omitted consecutively, or within the same cycle, BTZ should be restarted at a reduced dose
Anemia | Hb <8 g/dL CTCAE Grade 3
 | Interrupt FARYDAK until Hb ≥10 g/dL Restart at reduced dose.
Diarrhea | Moderate Diarrhea 4 to 6 stools/day CTCAE Grade 2 |  | Severe Diarrhea (≥7 stools/day) IV fluids or hospitalization required CTCAE Grade 3 | Life-threatening Diarrhea CTCAE Grade 4
 | Interrupt FARYDAK until resolved. Restart at same dose. |  | Interrupt FARYDAK until resolved. Restart at reduced dose. | Permanently discontinue FARYDAK
 | Consider Interruption of BTZ until resolved. Restart at same dose. |  | Interrupt BTZ until resolved. Restart at reduced dose. | Permanently discontinue BTZ
Nausea or Vomiting | Severe Nausea CTCAE Grade 3/4 |  | Severe / Life-threatening Vomiting CTCAE Grade 3/4
 | Interrupt FARYDAK until resolved, then restart at reduced dose. |  | Interrupt FARYDAK until resolved, then restart at reduced dose.
BTZ = bortezomib
ANC = absolute neutrophil count
Hb = hemoglobin
IV = intravenous

Myelosuppression

Interrupt or reduce the dose of FARYDAK in patients who have thrombocytopenia, neutropenia or anemia according to instructions in Table 3. For patients with severe thrombocytopenia, consider platelet transfusions [see Warnings and Precautions (5.4), Adverse Reactions (6.1)]. Discontinue FARYDAK treatment if thrombocytopenia does not improve despite the recommended treatment modifications or if repeated platelet transfusions are required.

In the event of Grade 3 or 4 neutropenia, consider dose reduction and/or the use of growth factors (e.g., G-CSF). Discontinue FARYDAK if neutropenia does not improve despite dose modifications, colony-stimulating factors, or in case of severe infection.

Gastrointestinal Toxicity

Gastrointestinal toxicity is common in patients treated with FARYDAK. Patients who experience diarrhea, nausea, or vomiting may require treatment interruption or dose reduction (Table 3). At the first sign of abdominal cramping, loose stools, or onset of diarrhea, patients should be treated with anti-diarrheal medication (e.g., loperamide). Consider and administer prophylactic anti-emetics as clinically indicated.

Other Adverse Drug Reactions

For patients experiencing Grade 3/4 adverse drug reactions other than thrombocytopenia, neutropenia, or gastrointestinal toxicity, the recommendation is the following:

- CTC Grade 2 toxicity recurrence and CTC Grade 3 and 4 - omit the dose until recovery to CTC Grade 1 or less and restart treatment at a reduced dose
- CTC Grade 3 or 4 toxicity recurrence, a further dose reduction may be considered once the adverse events have resolved to CTC Grade 1 or less.

2.4 Dose Modifications for Use in Hepatic Impairment

Reduce the starting dose of FARYDAK to 15 mg in patients with mild hepatic impairment and 10 mg in patients with moderate hepatic impairment. Avoid use in patients with severe hepatic impairment. Monitor patients frequently for adverse events and adjust dose as needed for toxicity [see Dosing and Administration (2.2), Warnings and Precautions (5.6), Hepatic Impairment (8.6), Clinical Pharmacology (12.3)].

2.5 Dose Modifications for Use with Strong CYP3A Inhibitors

Reduce the starting dose of FARYDAK to 10 mg when coadministered with strong CYP3A inhibitors (e.g., boceprevir, clarithromycin, conivaptan, indinavir, itraconazole, ketoconazole, lopinavir/ritonavir) [see Drug Interactions (7.1), Clinical Pharmacology (12.3)].

3 DOSAGE FORMS AND STRENGTHS

Capsules: 10 mg, 15 mg, and 20 mg panobinostat (equivalent to 12.58 mg, 18.86 mg, and 25.15 mg respectively of panobinostat lactate)

10 mg: Size #3 light green opaque capsule, radial markings on cap with black ink “LBH 10 mg” and two radial bands with black ink on body, containing white to almost white powder.

15 mg: Size #1 orange opaque capsule, radial markings on cap with black ink “LBH 15 mg” and two radial bands with black ink on body, containing white to almost white powder.

20 mg: Size #1 red opaque capsule, radial markings on cap with black ink “LBH 20 mg” and two radial bands with black ink on body, containing white to almost white powder.

4 CONTRAINDICATIONS

None

5 WARNINGS AND PRECAUTIONS

5.1 Diarrhea

Severe diarrhea occurred in 25% of patients treated with FARYDAK [see Adverse Reactions (6.1)]. Diarrhea of any grade occurred in 68% of patients treated with FARYDAK compared to 42% of patients in the control arm. Diarrhea can occur at any time. Monitor patient hydration status and electrolyte blood levels, including potassium, magnesium and phosphate, at baseline and weekly (or more frequently as clinically indicated) during therapy and correct to prevent dehydration and electrolyte disturbances. Initiate anti-diarrheal medication at the onset of diarrhea. Interrupt FARYDAK at the onset of moderate diarrhea (4 to 6 stools per day) [see Dosage and Administration (2.3)]. Ensure that patients initiating therapy with FARYDAK have anti-diarrheal medications on hand.

5.2 Cardiac Toxicities

Severe and fatal cardiac ischemic events, as well as severe arrhythmias, and electrocardiogram (ECG) changes occurred in patients receiving FARYDAK. Arrhythmias occurred in 12% of patients receiving FARYDAK, compared to 5% of patients in the control arm. Cardiac ischemic events occurred in 4% of patients treated with FARYDAK compared with 1% of patients in the control arm. Do not initiate FARYDAK treatment in patients with history of recent myocardial infarction or unstable angina.

Electrocardiographic abnormalities such as ST-segment depression and T-wave abnormalities also occurred more frequently in patients receiving FARYDAK compared to the control arm: 22% versus 4% and 40% versus 18%, respectively. FARYDAK may prolong cardiac ventricular repolarization (QT interval). Do not initiate treatment with FARYDAK in patients with a QTcF >450 msec or clinically significant baseline ST-segment or T-wave abnormalities. Arrhythmias may be exacerbated by electrolyte abnormalities. If during treatment with FARYDAK, the QTcF increases to ≥480 msec, interrupt treatment. Correct any electrolyte abnormalities. If QT prolongation does not resolve, permanently discontinue treatment with FARYDAK.

Obtain ECG at baseline and periodically during treatment as clinically indicated. Monitor electrolytes during treatment with FARYDAK and correct abnormalities as clinically indicated.

5.3 Hemorrhage

Fatal and serious hemorrhage occurred during treatment with FARYDAK. In the clinical trial in patients with relapsed multiple myeloma, 5 patients receiving FARYDAK compared to 1 patient in the control arm died due to a hemorrhagic event. All 5 patients had grade ≥3 thrombocytopenia at the time of the event. Grade 3/4 hemorrhage was reported in 4% of patients treated with the FARYDAK arm and 2% of patients in the control arm.

5.4 Myelosuppression

FARYDAK causes myelosuppression, including severe thrombocytopenia, neutropenia and anemia. In the clinical trial in patients with relapsed multiple myeloma, 67% of patients treated with FARYDAK developed Grade 3 to 4 thrombocytopenia compared with 31% in the control arm. Thrombocytopenia led to treatment interruption and or dose modification in 31% of patients receiving FARYDAK compared to 11% of patients in the control arm. For patients receiving FARYDAK, 33% required platelet transfusion compared to 10% of patients in the control arm [see Dosage and Administration (2.2)].

Severe neutropenia occurred in 34% of patients treated with FARYDAK, compared to 11% of patients in the control arm. Neutropenia led to treatment interruption and or dose modification in 10% of patients receiving FARYDAK. The use of granulocyte-colony stimulating factor (G-CSF) was higher in patients treated with FARYDAK compared to the control arm, 13% compared to 4%, respectively.

Obtain a baseline CBC and monitor the CBC weekly during treatment (or more frequently if clinically indicated). Dose modifications are recommended for Myelosuppression [see Dosage and Administration (2.2)]. Monitor CBCs more frequently in patients over 65 years of age due to the increased frequency of myelosuppression in these patients [see Use in Specific Populations (8.5)].

5.5 Infections

Localized and systemic infections, including pneumonia, bacterial infections, invasive fungal infections, and viral infections have been reported in patients taking FARYDAK. Severe infections occurred in 31% of patients (including 10 deaths) treated with FARYDAK compared with 24% of patients (including 6 deaths) in the control arm. Infections of all grades occurred at a similar rate between arms. FARYDAK treatment should not be initiated in patients with active infections. Monitor patients for signs and symptoms of infections during treatment; if a diagnosis of infection is made, institute appropriate anti-infective treatment promptly and consider interruption or discontinuation of FARYDAK.

5.6 Hepatotoxicity

Hepatic dysfunction, primarily elevations in aminotransferases and total bilirubin, occurred in patients treated with FARYDAK. Liver function should be monitored prior to treatment and regularly during treatment. If abnormal liver function tests are observed dose adjustments may be considered and the patient should be followed until values return to normal or pretreatment levels [see Dosage and Administration (2.4), Clinical Pharmacology (12.3)].

5.7 Embryo-Fetal Toxicity

FARYDAK can cause fetal harm when administered to a pregnant woman. Panobinostat was teratogenic in rats and rabbits. If FARYDAK is used during pregnancy, or if the patient becomes pregnant while taking FARYDAK, the patient should be apprised of the potential hazard to the fetus [see Use in Specific Populations (8.1, 8.3)].

Advise females of reproductive potential to avoid becoming pregnant while taking FARYDAK. Advise sexually-active females of reproductive potential to use effective contraception while taking FARYDAK and for at least 3 months after the last dose of FARYDAK.

Advise sexually active men to use condoms while on treatment and for 6 months after their last dose of FARYDAK [see Use in Specific Populations (8.3)].

6 ADVERSE REACTIONS

The following adverse reactions are described in detail in other sections of the label:

- Diarrhea [see Warnings and Precautions (5.1)]
- Cardiac Toxicities [see Warnings and Precautions (5.2)]
- Hemorrhage [see Warnings and Precautions (5.3)]
- Myelosuppression [see Warnings and Precautions (5.4)]
- Infections [see Warnings and Precautions (5.5)]
- Hepatotoxicity [see Warnings and Precautions (5.6)]

Because clinical trials are conducted under widely varying conditions, adverse reaction rates observed in the clinical trials of a drug cannot be directly compared to rates in the clinical trials of another drug and may not reflect the rates observed in practice.

6.1 Clinical Trials Experience

The safety data reflect subject exposure to FARYDAK from a clinical trial, in which 758 subjects with relapsed multiple myeloma received FARYDAK in combination with bortezomib and dexamethasone or placebo in combination with bortezomib and dexamethasone (referred to as the control arm). The median duration of exposure to FARYDAK was 5 months with 16% of patients exposed to study treatment for ≥48 weeks.

Serious adverse events (SAEs) occurred in 60% of patients in the FARYDAK, bortezomib, and dexamethasone compared to 42% of patients in the control arm. The most frequent (≥5%) treatment-emergent SAEs reported for patients treated with FARYDAK were pneumonia (18%), diarrhea, (11%), thrombocytopenia (7%), fatigue (6%), and sepsis (6%).

Adverse reactions that led to discontinuation of FARYDAK occurred in 36% of patients. The most common adverse reactions leading to treatment discontinuations were diarrhea, fatigue, and pneumonia.

Deaths occurred in 8% of patients in the FARYDAK arm versus 5% on the control arm. The most frequent causes of death were infection and hemorrhage.

Table 4 summarizes the adverse reactions occurring in at least 10% of patients with ≥ 5% greater incidence in the FARYDAK arm, and Table 5 summarizes the treatment-emergent laboratory abnormalities.

Table 4: Adverse Reactions (≥10% Incidence and ≥5% Greater Incidence in FARYDAK-Arm) in Patients with Multiple Myeloma
Primary System Organ Class Preferred term | FARYDAK, BTZ [1], Dex [2] N=381 All grades % | FARYDAK, BTZ [1], Dex [2] N=381 Grade 3/4 % | Placebo, BTZ [1], Dex [2] N=377 All grades % | Placebo, BTZ [1], Dex [2] N=377 Grade 3/4 %
Cardiac disorders
Arrhythmia[3] | 12 | 3 | 5 | 2
Gastrointestinal disorders
Diarrhea | 68 | 25 | 42 | 8
Nausea | 36 | 6 | 21 | 1
Vomiting | 26 | 7 | 13 | 1
General disorders and administration site conditions
Fatigue[4] | 60 | 25 | 42 | 12
Peripheral edema | 29 | 2 | 19 | <1
Pyrexia | 26 | 1 | 15 | 2
Investigations
Weight decreased | 12 | 2 | 5 | 1
Metabolism and nutrition disorders
Decreased appetite | 28 | 3 | 12 | 1
[1] BTZ = bortezomib
[2] Dex = dexamethasone
[3] Arrhythmia includes the terms: arrhythmia, arrhythmia supraventricular, atrial fibrillation, atrial flutter, atrial tachycardia, bradycardia, cardiac arrest, cardio-respiratory arrest, sinus bradycardia, sinus tachycardia, supraventricular extra-systoles, tachycardia, ventricular arrhythmia, and ventricular tachycardia
[4] Fatigue includes the terms: fatigue, malaise, asthenia, and lethargy

Other Adverse Reactions

Other notable adverse drug reactions of FARYDAK not described above, which were either clinically significant, or occurred with a frequency less than 10% but had a frequency in the FARYDAK arm greater than 2% over the control arm in the multiple myeloma clinical trial are listed below:

Infections and infestations: hepatitis B.

Endocrine disorders: hypothyroidism.

Metabolism and nutrition disorders: hyperglycemia, dehydration, fluid retention, hyperuricemia, hypomagnesemia.

Nervous system disorders: dizziness, headache, syncope, tremor, dysgeusia.

Cardiac disorders: palpitations.

Vascular disorders: hypotension, hypertension, orthostatic hypotension.

Respiratory, thoracic and mediastinal disorders: cough, dyspnea, respiratory failure, rales, wheezing.

Gastrointestinal disorders: abdominal pain, dyspepsia, gastritis, cheilitis, abdominal distension, dry mouth, flatulence, colitis, gastrointestinal pain.

Skin and subcutaneous disorders: skin lesions, rash, erythema.

Musculoskeletal and connective tissue disorders: joint swelling.

Renal and urinary disorders: renal failure, urinary incontinence.

General disorders and administration site conditions: chills.

Investigations: blood urea increased, glomerular filtration rate decreased, blood alkaline phosphatase increased.

Psychiatric disorders: insomnia.

Table 5: Treatment-emergent Laboratory Abnormalities (≥10% Incidence and ≥5% Greater Incidence in FARYDAK-arm) in Patients with Multiple Myeloma
Investigations | FARYDAK, BTZ[1], Dex[2] N=381 Any grade % | FARYDAK, BTZ[1], Dex[2] N=381 Grade 3/4 % | Placebo, BTZ[1], Dex[2] N=377 Any grade % | Placebo, BTZ[1], Dex[2] N=377 Grade 3/4 %
Hematology
Thrombocytopenia | 97 | 67 | 83 | 31
Anemia | 62 | 18 | 52 | 19
Neutropenia | 75 | 34 | 36 | 11
Leukopenia | 81 | 23 | 48 | 8
Lymphopenia | 82 | 53 | 74 | 40
Chemistry
Blood creatinine increased | 41 | 1 | 23 | 2
Hypokalemia | 52 | 18 | 36 | 7
Hypophosphatemia | 63 | 20 | 45 | 12
Hyponatremia | 49 | 13 | 36 | 7
Hyperbilirubinemia | 21 | 1 | 13 | <1
Hypocalcemia | 67 | 5 | 55 | 2
Hypoalbuminemia | 63 | 2 | 38 | 2
Hyperphosphatemia | 29 | 2 | 20 | <1
Hypermagnesemia | 27 | 5 | 14 | 1
[1] BTZ = bortezomib
[2] Dex = dexamethasone

Fatigue and Asthenia

Grade 1 to Grade 4 asthenic conditions (fatigue, malaise, asthenia, and lethargy) were reported in 60% of the patients in the FARYDAK arm compared to 42% of patients in the control arm. Grade ≥3 asthenic conditions were reported in 25% of the patients in the FARYDAK arm compared to 12% of patients in the control arm. Asthenic conditions led to treatment discontinuation in 6% of patients in the FARYDAK arm versus 3% of patients in the control arm.

The prespecified sub-group upon which the efficacy and safety of FARYDAK was based had a similar adverse reaction profile to the entire safety population of patients treated with FARYDAK, bortezomib, and dexamethasone.

7 DRUG INTERACTIONS

Panobinostat is a CYP3A substrate and inhibits CYP2D6. Panobinostat is a P-glycoprotein (P-gp) transporter system substrate.

7.1 Agents that May Increase FARYDAK Blood Concentrations

CYP3A Inhibitors: Coadministration of FARYDAK with a strong CYP3A inhibitor increased the Cmax and AUC of panobinostat by 62% and 73% respectively, compared to when FARYDAK was given alone [see Clinical Pharmacology (12.3)].

Reduce dose to 10 mg when coadministered with strong CYP3A inhibitors (e.g., boceprevir, clarithromycin, conivaptan, indinavir, itraconazole, ketoconazole, lopinavir/ritonavir, nefazodone, nelfinavir, posaconazole, ritonavir, saquinavir, telaprevir, telithromycin, voriconazole) [see Dosage and Administration (2.5)]. Instruct patients to avoid star fruit, pomegranate or pomegranate juice, and grapefruit or grapefruit juice because these foods are known to inhibit CYP3A enzymes.

7.2 Agents that May Decrease FARYDAK Plasma Concentrations

CYP3A Inducers: Coadministration of FARYDAK with strong CYP3A inducers was not evaluated in vitro or in a clinical trial however, a reduction in panobinostat exposure is likely. An approximately 70% decrease in the systemic exposure of panobinostat in the presence of strong inducers of CYP3A was observed in simulations using mechanistic models. Therefore, the concomitant use of strong CYP3A inducers should be avoided [see Clinical Pharmacology (12.3)].

7.3 Agents whose Plasma Concentrations May be Increased by FARYDAK

CYP2D6 Substrates: FARYDAK increased the median Cmax and AUC of a sensitive substrate of CYP2D6 by approximately 80% and 60%, respectively; however this was highly variable [see Clinical Pharmacology (12.3)]. Avoid coadministrating FARYDAK with sensitive CYP2D6 substrates (i.e., atomoxetine, desipramine, dextromethorphan, metoprolol, nebivolol, perphenazine, tolterodine, and venlafaxine) or CYP2D6 substrates that have a narrow therapeutic index (i.e., thioridazine, pimozide). If concomitant use of CYP2D6 substrates is unavoidable, monitor patients frequently for adverse reactions.

7.4 Drugs that Prolong QT interval

Concomitant use of anti-arrhythmic medicines (including, but not limited to amiodarone, disopyramide, procainamide, quinidine and sotalol) and other drugs that are known to prolong the QT interval (including, but not limited to chloroquine, halofantrine, clarithromycin, methadone, moxifloxacin, bepridil and pimozide) is not recommended. Anti-emetic drugs with known QT prolonging risk, such as dolasetron, ondansetron, and tropisetron can be used with frequent ECG monitoring [see Warnings and Precautions (5.2)].

8 USE IN SPECIFIC POPULATIONS

8.1 Pregnancy

Risk Summary

FARYDAK can cause fetal harm when administered to a pregnant woman. Panobinostat was teratogenic in rats and rabbits. If FARYDAK is used during pregnancy or if the patient becomes pregnant while taking this drug, apprise the patient of the potential hazard to the fetus.

Data

Animal Data

In embryofetal development studies, panobinostat was administered orally 3 times per week during the period of organogenesis to pregnant rats (30, 100, and 300 mg/kg) and rabbits (10, 40, and 80 mg/kg). In rats, maternal toxicity including death was observed at doses greater than or equal to 100 mg/kg/day. Embryofetal toxicities occurred at 30 mg/kg (the only dose with live fetuses) and consisted of fetal malformations and anomalies, such as cleft palate, short tail, extra presacral vertebrae, and extra ribs. The dose of 30 mg/kg resulted in exposures (AUCs) approximately 3-fold the human exposure at the human dose of 20 mg. In rabbits, maternal toxicity including death was observed at doses greater than or equal to 80 mg/kg. Increased pre- and/or post-implantation loss occurred at all doses tested. Embryofetal toxicities included decreased fetal weights at doses greater than or equal to 40 mg/kg and malformations (absent digits, cardiac interventricular septal defects, aortic arch interruption, missing gallbladder, and irregular ossification of skull) at 80 mg/kg. The dose of 40 mg/kg in rabbits results in systemic exposure approximately 4-fold the human exposure and the dose of 80 mg/kg results in exposure 7-fold the human exposure, at the human dose of 20 mg.

8.2 Lactation

Risk Summary

It is not known whether FARYDAK is excreted in human milk. Because many drugs are excreted in human milk and because of the potential for serious adverse drug reactions in nursing infants, decide whether to discontinue nursing or to discontinue the drug, taking into account the importance of the drug to the mother.

8.3 Females and Males of Reproductive Potential

Embryofetal toxicity including malformations occurred in embryofetal development studies in rats [see Pregnancy (8.1)].

Pregnancy Testing

Perform pregnancy testing in women of childbearing potential prior to starting treatment with FARYDAK and intermittently during treatment with FARYDAK.

Contraception

Females

FARYDAK can cause fetal harm. Advise females of reproductive potential to avoid becoming pregnant while taking FARYDAK. Advise sexually-active females of reproductive potential to use effective contraception while taking FARYDAK and for at least 3 months after the last dose of FARYDAK. Advise patients to contact their healthcare provider if they become pregnant, or if pregnancy is suspected, while taking FARYDAK [see Use in Specific Populations (8.1)].

Males

Advise sexually active men to use condoms while on treatment and for at least 6 months after their last dose of FARYDAK.

8.4 Pediatric Use

The safety and efficacy of FARYDAK in children has not been established.

8.5 Geriatric Use

In clinical trials of FARYDAK in patients with multiple myeloma, 42% of patients were 65 years of age or older.

Patients over 65 years of age had a higher frequency of selected adverse events and of discontinuation of treatment due to adverse events. In patients over 65 years of age, the incidence of deaths not related to disease progression was 9% in patients ≥65 years of age compared to 5 % in patients <65.

In the randomized clinical trial in patients with relapsed multiple myeloma, no major differences in effectiveness were observed in older patients compared to younger patients. Adverse reactions leading to permanent discontinuation occurred in 45% of patients ≥65 years of age in the FARYDAK treatment arm compared to 30% of patients <65 years age in the FARYDAK treatment arm. Monitor for toxicity more frequently in patients over 65 years of age, especially for gastrointestinal toxicity, myelosuppression, and cardiac toxicity [see Warnings and Precautions (5.1, 5.4)].

8.6 Hepatic Impairment

The safety and efficacy of FARYDAK in patients with hepatic impairment has not been evaluated.

In a pharmacokinetic trial, patients with mild (bilirubin ≤1xULN and AST >1xULN, or bilirubin >1.0 to 1.5x ULN and any AST) or moderate (bilirubin >1.5x to 3.0x ULN, any AST) hepatic impairment (NCI-ODWG criteria) had increased AUC of panobinostat by 43% and 105%, respectively. Reduce the starting dose of FARYDAK in patients with mild or moderate hepatic impairment. Avoid use in patients with severe hepatic impairment. Monitor patients with hepatic impairment frequently for adverse events [see Dosage and Administration (2.4), Warnings and Precautions (5.6), Clinical Pharmacology (12.3)].

8.7 Renal Impairment

Mild [creatinine clearance (CrCl) ≥50 to <80 mL/min] to severe renal impairment (CrCl <30 mL/min) did not impact the plasma exposure of panobinostat. FARYDAK has not been studied in patients with end stage renal disease (ESRD) or patients on dialysis. The dialyzability of panobinostat is unknown [see Clinical Pharmacology (12.3)].

10 OVERDOSAGE

There is limited experience with overdosage. Expect exaggeration of adverse reactions observed during the clinical trial, including hematologic and gastrointestinal reactions such as thrombocytopenia, pancytopenia, diarrhea, nausea, vomiting and anorexia. Monitor cardiac status including ECGs, and assess and correct electrolytes. Consider platelet transfusions for thrombocytopenic bleeding. It is not known if FARYDAK is dialyzable.

11 DESCRIPTION

FARYDAK (panobinostat lactate) is a histone deacetylase inhibitor.

The chemical name of panobinostat lactate is 2-Hydroxypropanoic acid, compd. with 2-(E)-N-hydroxy-3-[4-[[[2-(2-methyl-1H-indol-3-yl)ethyl]amino]methyl]phenyl]-2-propenamide (1:1).

The structural formula is:

Panobinostat lactate anhydrous is a white to slightly yellowish or brownish powder. The molecular formula is C21H23N3O2•C3H6O3 (lactate); its molecular weight is 439.51 (as a lactate), equivalent to 349.43 (free base). Panobinostat lactate anhydrous is light sensitive. Panobinostat lactate anhydrous is both chemically and thermodynamically a stable crystalline form with no polymorphic behavior. Panobinostat free base is not chiral and shows no specific optical rotation. Panobinostat lactate anhydrous is slightly soluble in water. Solubility of panobinostat lactate anhydrous is pH-dependent, with the highest solubility in buffer pH 3.0 (citrate).

FARYDAK capsules contain 10 mg, 15 mg, or 20 mg panobinostat free base (equivalent to 12.58 mg, 18.86 mg, and 25.15 mg respectively of panobinostat lactate). The inactive ingredients are magnesium stearate, mannitol, microcrystalline cellulose and pregelatinized starch. The capsules contain gelatin, FD&C Blue 1 (10 mg capsules), yellow iron oxide (10 mg and 15 mg capsules), red iron oxide (15 mg and 20 mg capsules) and titanium dioxide.

12 CLINICAL PHARMACOLOGY

12.1 Mechanism of Action

FARYDAK is a histone deacetylase (HDAC) inhibitor that inhibits the enzymatic activity of HDACs at nanomolar concentrations. HDACs catalyze the removal of acetyl groups from the lysine residues of histones and some non-histone proteins. Inhibition of HDAC activity results in increased acetylation of histone proteins, an epigenetic alteration that results in a relaxing of chromatin, leading to transcriptional activation. In vitro, panobinostat caused the accumulation of acetylated histones and other proteins, inducing cell cycle arrest and/or apoptosis of some transformed cells. Increased levels of acetylated histones were observed in xenografts from mice that were treated with panobinostat. Panobinostat shows more cytotoxicity towards tumor cells compared to normal cells.

12.2 Pharmacodynamics

Cardiac Electrophysiology

FARYDAK may prolong cardiac ventricular repolarization (QT interval) [see Warnings and Precautions (5.2)]. In the randomized multiple myeloma trial, QTc prolongation with values between 451 msec to 480 msec occurred in 10.8% of FARYDAK treated patients. Events with values of 481 msec to 500 msec occurred in 1.3% of FARYDAK treated patients. A maximum QTcF increase from baseline of between 31 msec and 60 msec was reported in 14.5% of FARYDAK treated patients. A maximum QTcF increase from baseline of >60 msec was reported in 0.8% of FARYDAK treated patients. No episodes of QTcF prolongation >500 msec have been reported with the dose of 20 mg FARYDAK in the randomized multiple myeloma trial conducted in combination with bortezomib and dexamethasone. Pooled clinical data from over 500 patients treated with single agent FARYDAK in multiple indications and at different dose levels has shown that the incidence of CTC Grade 3 QTc prolongation (QTcF >500 msec) was approximately 1% overall and 5% or more at a dose of 60 mg or higher.

12.3 Pharmacokinetics

Absorption

The absolute oral bioavailability of FARYDAK is approximately 21%. Peak concentrations of panobinostat are observed within 2 hours (Tmax) of oral administration in patients with advanced cancer. FARYDAK exhibits an approximate dose proportional increase in both Cmax and AUC over the dosing range.

Plasma panobinostat Cmax and AUC0–48 were approximately 44% and 16% lower compared to fasting conditions, respectively, following ingestion of an oral FARYDAK dose 30 minutes after a high-fat meal by 36 patients with advanced cancer. The median Tmax was also delayed by 2.5 hours in these patients.

The aqueous solubility of panobinostat is pH dependent, with higher pH resulting in lower solubility [see Description (11)]. Coadministration of FARYDAK with drugs that elevate the gastric pH was not evaluated in vitro or in a clinical trial; however, altered panobinostat absorption was not observed in simulations using physiologically-based pharmacokinetic (PBPK) models.

Distribution

Panobinostat is approximately 90% bound to human plasma proteins in vitro and is independent of concentration. Panobinostat is a P-gp substrate.

Metabolism

Panobinostat is extensively metabolized. Pertinent metabolic pathways involved in the biotransformation of panobinostat are reduction, hydrolysis, oxidation, and glucuronidation processes. The fraction metabolized through CYP3A accounts for approximately 40% of the total hepatic panobinostat elimination. In vitro, additional contributions from the CYP2D6 and CYP2C19 pathways are minor. In vitro, UGT1A1, UGT1A3, UGT1A7, UGT1A8, UGT1A9, and UGT2B4 contribute to the glucuronidation of panobinostat.

Elimination

Twenty-nine percent to 51% of administered radioactivity is excreted in urine and 44% to 77% in the feces after a single oral dose of [^14C] panobinostat in 4 patients with advanced cancer. Unchanged panobinostat accounted for <2.5% of the dose in urine and <3.5% of the dose in feces with the remainder consisting of metabolites.

An oral clearance (CL/F) and terminal elimination half-life (t1/2) of approximately 160 L/hr and 37 hours, respectively, was estimated using a population based pharmacokinetic (pop-PK) model in patients with advanced cancer. An inter-subject variability 65% on the clearance estimate was also reported. Up to 2-fold accumulation was observed with chronic oral dosing in patients with advanced cancer.

Specific Populations

Population pharmacokinetic (PK) analyses of FARYDAK indicated that body surface area, gender, age, and race do not have a clinically meaningful influence on clearance.

Hepatic Impairment: The effect of hepatic impairment on the pharmacokinetics of panobinostat was evaluated in a phase 1 study in 24 patients with advanced cancer with varying degrees of hepatic impairment. In patients with NCI-CTEP class mild (i.e., Group B) and moderate (i.e., Group C) hepatic impairment, AUC0-inf increased 43% and 105% compared to the group with normal hepatic function, respectively. The relative change in Cmax followed a similar pattern. The effect of severe hepatic impairment was indeterminate in this study due to the small sample size (n=1). A dose modification is recommended for patients with mild and moderate hepatic impairment [see Use in Specific Populations (8.6)].

Renal Impairment: The effect of renal impairment on the pharmacokinetics of panobinostat was assessed in a phase 1 trial of 37 patients with advanced cancer and varying degrees of renal impairment. Panobinostat AUC0–inf in the mild, moderate and severe renal impairment groups were 64%, 99% and 59%, of the normal group, respectively. The relative change in Cmax followed a similar pattern [see Use in Specific Populations (8.7)].

Drug Interactions:

Strong CYP3A Inhibitors: Coadministration of a single 20 mg FARYDAK dose with ketoconazole (200 mg twice daily for 14 days) increased the Cmax and AUC0–48 of panobinostat by 62% and 73% respectively, compared to when FARYDAK was given alone in 14 patients with advanced cancer. Tmax was unchanged. A modified starting dose is recommended [see Dose and Administration (2.4), Drug Interactions (7.1)].

Strong CYP3A Inducers: The human oxidative metabolism of panobinostat via the cytochrome P450 system primarily involves CYP3A isozymes. Simulations using PBPK models, predicted an approximately 70% decrease in the systemic exposure of panobinostat in the presence of strong inducers of CYP3A. Avoid coadministration of FARYDAK with strong CYP3A inducers [see Drug Interactions (7.2)].

CYP2D6 Substrates: Coadministration of a single 60 mg dextromethorphan (DM) dose with FARYDAK (20 mg once per day, on Days 3, 5, and 8) increased the Cmax and AUC0–∞ of DM by 20% to 200% and 20% to 130% (interquartile ranges), respectively, compared to when DM was given alone in 14 patients with advanced cancer. These DM exposures were extremely variable (CV% >150%). Avoid coadministration of FARYDAK with sensitive CYP2D6 substrates or CYP2D6 substrates that have a narrow therapeutic index [see Drug Interactions (7.3)].

CYP3A Substrates: Simulations using PBPK models predict that an exposure increase of less than 10% for the sensitive CYP3A substrate midazolam is likely following coadministration with panobinostat. The clinical implications of this finding are not known.

In vitro studies with CYP or UDPglucuronosyltransferase (UGT) substrates:

Panobinostat inhibits CYP2D6, CYP2C19 and CYP3A4 (time-dependent), but does not inhibit CYP1A2, CYP2C8, CYP2C9, and CYP2E. Panobinostat does not induce CYP1A1/2, CYP2B6, CYP2C8/9/19, CYP3A and UGT1A1.

In vitro studies with drug transporter system substrates:

Panobinostat inhibits OAT3, OCT1, OCT2, OATP1B1 and OATP1B3, but does not inhibit P-gp and breast cancer resistant protein (BCRP), or OAT1.

Panobinostat does not induce P-gp and multidrug resistance protein 2 (MRP2) transporters.

13 NONCLINICAL TOXICOLOGY

13.1 Carcinogenesis, Mutagenesis, Impairment of Fertility

Carcinogenicity studies have not been conducted with panobinostat.

Panobinostat was mutagenic in the Ames assay, and caused endo-reduplication (increased number of chromosomes) in human peripheral blood lymphocytes in vitro and DNA damage in an in vitro COMET assay in mouse lymphoma L5178Y cells.

FARYDAK may impair male and female fertility. In an oral fertility study conducted in rats, 10, 30, or 100 mg/kg doses of panobinostat were administered to females 3 times weekly (Days 1, 3, and 5) for 2 weeks prior to mating, then during the mating period, and on gestation Days 0, 3, and 6. An increase in early resorption and/or post-implantation loss in female rats were observed at doses ≥10 mg/kg. Number of pregnancies was reduced at doses ≥30 mg/kg. Prostate atrophy accompanied by reduced secretory granules, and testicular degeneration, oligospermia and increased epididymal debris were observed in repeated dose oral toxicity studies in dogs, e.g., in the 4-week study at the dose of 1.5 mg/kg. These effects were not completely reversed following a 4-week nondosing period.

13.2 Animal Toxicology and/or Pharmacology

Adverse findings observed in animals and not reported (or reported with low incidence) in patients treated with panobinostat include thyroid, bone marrow, and skin findings. Thyroid hormone changes in oral studies in rats and dogs included decreases in triodothyronine (T3), tetraiodothyronine (T4) and thyroid stimulating hormone (TSH). Histopathology changes of the thyroid included decreases in follicular colloid and epithelial vacuolation, and increases in thyroid follicular hypertrophy. A benign thyroid follicular cell adenoma was also seen in 1 rat in the 26-week study. Bone marrow findings in one or both species included hyperostosis, plasmacytosis, increased number of granulocytic cells, and presence of abnormal cytoplasmic granulation. Osseous metaplasia of the lung and skin hyperplasia and papilloma were observed in dogs in the 39-week study.

14 CLINICAL STUDIES

14.1 Relapsed Multiple Myeloma

The efficacy and safety of FARYDAK in combination with bortezomib and dexamethasone was evaluated in a randomized, double-blind, placebo-controlled, multicenter study in patients with relapsed multiple myeloma who had received 1 to 3 prior lines of therapy.

Patients received bortezomib (1.3 mg/m^2 injected intravenously) with dexamethasone (20 mg) in addition to FARYDAK 20 mg (or placebo), taken orally every other day, for 3 doses per week in Weeks 1 and 2 of each 21-day cycle. Treatment was administered for a maximum of 16 cycles (48 weeks).

A total of 768 patients were randomized in a 1:1 ratio to receive either the combination of FARYDAK, bortezomib, dexamethasone (n=387) or placebo, bortezomib, dexamethasone (n=381), stratified by prior use of bortezomib and the number of prior lines of anti-myeloma therapy. Demographics and baseline disease characteristics were balanced between arms. The median age was 63 years (range 28 to 84); 42% of patients were older than 65 years; 53% of patients were male; Caucasians comprised 65% of the study population, Asians 30%, and blacks 3%. The ECOG performance status was 0 to 1 in 93% of patients. The median number of prior therapies was 1; 48% of patients received 2 or 3 prior lines of therapy. More than half (57%) of the patients had prior stem cell transplantation. The most common prior antineoplastic therapies were corticosteroids (90%), melphalan (80%), thalidomide (53%), cyclophosphamide (47%), bortezomib (44%), and lenalidomide (19%). The median duration of follow-up was 29 months in both arms.

The primary endpoint was progression-free survival (PFS), using modified European Bone Marrow Transplant Group (EBMT) criteria, as assessed by the investigators. In the overall trial population, the median PFS (95% CI) was 12 months (10.3, 12.9) in the FARYDAK, bortezomib, dexamethasone arm and 8.1 months (7.6, 9.2) in the placebo, bortezomib, dexamethasone arm, [HR: 0.63 (95% CI: 0.52, 0.76)]. At the time of interim analysis, overall survival was not statistically different between arms. The approval of FARYDAK was based upon the efficacy and safety in a prespecified subgroup analysis of 193 patients who had received prior treatment with both bortezomib and an immunomodulatory agent and a median of 2 prior therapies as the benefit:risk appeared to be greater in this more heavily pretreated population than in the overall trial population. Of these 193 patients, 76% of them had received ≥2 prior lines of therapy. The median PFS (95% CI) was 10.6 months (7.6, 13.8) in the FARYDAK, bortezomib, and dexamethasone arm and 5.8 months (4.4, 7.1) in the placebo, bortezomib, and dexamethasone arm [HR: 0.52 (0.36, 0.76]. Efficacy results are summarized in Table 6 and the Kaplan- Meier curves for PFS are provided in Figure 1.

Table 6: Efficacy Results from the Multiple Myeloma Trial in Patients who Received Prior Treatment with Bortezomib and an Immunomodulating Agent
 | FARYDAK bortezomib and dexamethasone N=94 | Placebo bortezomib and dexamethasone N=99
Progression-free Survival
Median, months [95% CI] | 10.6 [7.6, 13.8] | 5.8 [4.4, 7.1]
Hazard ratio [95% CI]^1 | 0.52 (0.36, 0.76)
^1 Hazard ratio obtained from stratified Cox model

Figure 1: Kaplan-Meier Plot of Progression-Free Survival in Patients with Multiple Myeloma who Received Prior Treatment with Both Bortezomib and an Immunomodulatory Agent

In the subgroup of patients who had received prior treatment with both bortezomib and an immunomodulatory agent (n=193), the overall response rate using modified EBMT criteria was 59% in the FARYDAK, bortezomib, and dexamethasone arm and 41% in the placebo, bortezomib, and dexamethasone arm. Response rates are summarized in Table 7.

Table 7: Response Rates
 | FARYDAK bortezomib and dexamethasone N=94 | Placebo bortezomib and dexamethasone N=99
Overall response | 55 (58.5%) | 41 (41.4%)
[95% CI] | (47.9, 68.6) | (31.6, 51.8)
Complete response | 8 (8.5%) | 2 (2.0%)
Near complete response | 13 (13.8%) | 7 (7.1%)
Partial response | 34 (36.2%) | 32 (32.3%)

15 REFERENCES

1. OSHA Hazardous Drugs. OSHA. http://www.osha.gov/SLTC/hazardousdrugs/index.html

16 HOW SUPPLIED/STORAGE AND HANDLING

How Supplied

FARYDAK 10 mg panobinostat (equivalent to 12.58 mg of panobinostat lactate): Size # 3 light green opaque capsule, radial markings on cap with black ink “LBH 10 mg” and two radial bands with black ink on body, containing white to almost white powder.

FARYDAK 15 mg panobinostat (equivalent to 18.86 mg of panobinostat lactate): Size #1 orange opaque capsule, radial markings on cap with black ink “LBH 15 mg” and two radial bands with black ink on body, containing white to off-white powder.

FARYDAK 20 mg panobinostat (equivalent to 25.15 mg of panobinostat lactate): Size #1 red opaque capsule, radial markings on cap with black ink “LBH 20 mg” and two radial bands with black ink on body, containing white to off-white powder.

FARYDAK capsules are packaged in PVC/PCTFE blister packs.

10 mg

Blister packs containing 6 capsules ………………………….…….NDC 73116-100-06

15 mg

Blister packs containing 6 capsules ………………………….…….NDC 73116-101-06

20 mg

Blister packs containing 6 capsules ………………………….…….NDC 73116-102-06

Storage and Handling

Store at 20°C to 25°C (68°F to 77°F), excursions permitted between 15°C and 30°C (59°F and 86°F). Store blister pack in original carton to protect from light. FARYDAK capsules should not be opened, crushed, or chewed. Direct contact of the powder in FARYDAK capsules with the skin or mucous membranes should be avoided. If such contact occurs wash thoroughly. Personnel should avoid exposure to crushed and/or broken capsules.

FARYDAK is a cytotoxic drug. Follow special handling and disposal procedures [see References (15)^1].

17 PATIENT COUNSELING INFORMATION

Advise the patient to read the FDA-approved patient labeling (Medication Guide).

Dosing and Administration

Instruct patients to take FARYDAK exactly as prescribed and not to change their dose or to stop taking FARYDAK unless they are told to do so by their healthcare provider. If a patient misses a dose, advise them to take their dose as soon possible and up to 12 hours after the specified dose time. If vomiting occurs advise the patient not to repeat the dose, but to take the next usual prescribed dose on schedule.

Cardiac Toxicity/Electrocardiographic Changes

Inform patients to report chest pain or discomfort, changes in heart beat (fast or slow), palpitations, lightheadedness, fainting, dizziness, blue discoloration of lips, shortness of breath, and swelling of lower limbs or skin as these may be warning signs of a heart problem.

Bleeding Risk

Inform patients that FARYDAK is associated with thrombocytopenia. Advise patients to contact their healthcare provider right away if they experience any signs of bleeding and inform patients that it might take longer than usual for them to stop bleeding. Advise patients of the need to monitor blood chemistry and hematology prior to the start of FARYDAK therapy and periodically thereafter.

Infections

Inform patients of the risk of neutropenia and severe and life-threatening infections. Instruct patients to contact their physician immediately if they develop a fever and/or any exhibit any signs of infection.

Gastrointestinal Toxicities

Inform patients that FARYDAK can cause severe nausea, vomiting and diarrhea which may require medication for treatment. Advise patients to contact their physician at the start of diarrhea, for persistent vomiting, or signs of dehydration. Inform patients to consult with their physicians prior to using medications with laxative properties.

Pregnancy

Inform patients that FARYDAK can cause fetal harm. Advise women of reproductive potential to avoid pregnancy while taking FARYDAK. Advise women of reproductive potential to use effective contraception while taking FARYDAK and for at least 3 months after the last dose of the drug.

Advise sexually active men to use condoms while receiving FARYDAK and for at least 6 months following the last dose of the drug.

Lactation

Advise women not to breastfeed while taking FARYDAK.

Distributed by:

Secura Bio, Inc.

Las Vegas, NV 89134

©Secura Bio

USFPR1900101

September 2019

MEDICATION GUIDE
FARYDAK® (FAYR-ah-dak)
(panobinostat) capsules

What is the most important information I should know about FARYDAK?
FARYDAK can cause serious side effects, including:
• Diarrhea is common with FARYDAK and can be severe. Tell your healthcare provider right away if you have abdominal (stomach) cramps, loose stool, diarrhea, or if you feel like you are becoming dehydrated. Your healthcare provider may prescribe medicines to help prevent or treat these side effects. Taking or using stool softeners or laxative medicines may worsen diarrhea, talk to your healthcare provider before taking or using these medicines.
Your healthcare provider will do regular tests to check the levels of fluid and electrolytes in your blood during treatment with FARYDAK.
• Heart problems. FARYDAK can cause severe heart problems which can lead to death. Your risk of heart problems may be increased if you have a condition called “long QT syndrome” or other heart problems. Your healthcare provider will do blood tests to check your electrolytes and do an electrocardiogram (ECG) tests before and during treatment with FARYDAK. Call your healthcare provider and get emergency medical help right away if you have any of the following symptoms of heart problems:

o chest pain

o dizziness

o faster or slower heart beat

o blue colored lips

o palpitations (feel like your heart is racing)

o shortness of breath

o feel lightheaded or faint

o swelling in your legs

• Bleeding. FARYDAK can cause severe bleeding which can lead to death. It may take you longer than usual to stop bleeding while you are taking FARYDAK. Your healthcare provider will check your platelet counts before you start FARYDAK and during your treatment with FARYDAK. Tell your healthcare provider right away if you get any of the following signs of bleeding:

o blood in your stools or black stools (look like tar)

o increased bruising

o pink or brown urine

o feeling dizzy or weak

o unexpected bleeding or bleeding that is severe or that you cannot control

o confusion

o vomit blood or vomit looks like coffee grounds

o change in your speech

o cough up blood or blood clots

o headache that lasts a long time

What is FARYDAK?
FARYDAK is a prescription medicine used, in combination with bortezomib and dexamethasone, to treat people with a type of cancer called multiple myeloma after at least 2 other types of treatment have been tried.
It is not known if FARYDAK is safe and effective in children.

What should I tell my healthcare provider before taking FARYDAK?
Before you take FARYDAK, tell your healthcare provider about all of your medical conditions, including if you:
• have diarrhea
• have heart problems
• have a history of bleeding problems
• have an infection. You should not take FARYDAK if you have an infection.
• have liver problems
• are pregnant or plan to become pregnant. FARYDAK can harm your unborn baby. You should not become pregnant during treatment with FARYDAK.
• If you become pregnant while taking FARYDAK, or think you may be pregnant, tell your healthcare provider right away.
o Females who are able to become pregnant should use effective birth control during treatment with FARYDAK and for at least 3 months after the last dose of FARYDAK.
o Males who are sexually active should use a condom during treatment with FARYDAK and for at least 6 months after the last dose of FARYDAK.
• are breastfeeding or plan to breastfeed. It is not known if FARYDAK will pass into your breast milk. You and your healthcare provider should decide if you will take FARYDAK or breastfeed. You should not do both.
Tell your healthcare provider about all of the medicines you take, including prescription and over-the-counter medicines, vitamins, and herbal supplements. Know the medicines you take. Keep a list of them to show your healthcare provider and pharmacist when you get a new medicine.

How should I take FARYDAK?
• Take FARYDAK exactly as your healthcare provider tells you to take it.
• Your healthcare provider will tell you how much FARYDAK to take and when to take it.
• Your healthcare provider may change your dose or stop treatment temporarily if you have side effects. Do not change your dose or stop taking FARYDAK without first talking with your healthcare provider.
• Take FARYDAK 1 time on each scheduled day at about the same time.
• FARYDAK can be taken with or without food.
• FARYDAK capsule should be swallowed whole with a cup of water. Do not open, crush, or chew FARYDAK.
• Avoid contact of the powder in the FARYDAK capsules. If you accidentally get powder from the FARYDAK capsule on your skin, wash the area with soap and water. If you accidentally get powder from the FARYDAK capsule in your eyes, flush your eyes with water.
• If you miss a dose of FARYDAK, take it as soon possible, up to 12 hours after the time the dose should have been taken.
• If you vomit after taking FARYDAK, do not take another capsule. Stay on your dosing schedule and take your next dose as usual.
• If you take too much FARYDAK, call your healthcare provider.

What should I avoid while taking FARYDAK?
• Avoid eating star fruit, pomegranate or pomegranate juice, and grapefruit or grapefruit juice while taking FARYDAK. These foods may affect the amount of FARYDAK in your blood.

What are the possible side effects of FARYDAK?
FARYDAK may cause serious side effects, including:
• See “What is the most important information I should know about FARYDAK?”
• Low blood cell counts are common with FARYDAK and can be severe. Your healthcare provider will check your blood counts before you start FARYDAK and during your treatment with FARYDAK.
o Low platelet count (thrombocytopenia) can cause unusual bleeding or bruising under your skin.
o Low white cell count (neutropenia) can cause you to get infections.
o Low red blood cell count (anemia) may make you feel weak, tired, or you may get tired easily, you look pale, or you feel short of breath.
• Infections. There is an increased risk of infection while taking FARYDAK. Contact your healthcare provider right away if you have a fever or have any signs of an infection:

o sweats or chills

o blood in your phlegm

o cough

o sores on your body

o flu-like symptoms

o warm or painful areas on your body

o shortness of breath

o feeling very tired

• Liver problems (hepatotoxicity). Your healthcare provider should do blood tests to check your liver before you start taking FARYDAK and if you have symptoms of liver problems while you take FARYDAK. Call your healthcare provider right away if you have the following symptoms of liver problems:

o feel tired or weak

o upper abdominal (stomach) pain

o loss of appetite

o yellowing of your skin or the white of your eyes

o Dark amber colored urine

The most common side effects of FARYDAK include tiredness, nausea, swelling in your arms or legs, decreased appetite, fever, and vomiting.
Tell your healthcare provider if you have any side effect that bothers you or that does not go away.
These are not all of the possible side effects of FARYDAK. For more information, ask your healthcare provider or pharmacist.
Call your doctor for medical advice about side effects. You may report side effects to FDA at 1-800-FDA-1088.

How should I store FARYDAK?
• Store FARYDAK between 68°F to 77°F (20°C to 25°C). Store blister pack in original carton to protect from light.
Keep FARYDAK and all medicines out of the reach of children.

General information about the safe and effective use of FARYDAK
Medicines are sometimes prescribed for purposes other than those listed in a Patient Information leaflet. Do not use FARYDAK for a condition for which it was not prescribed. Do not give FARYDAK to other people, even if they have the same symptoms that you have. It may harm them. You can ask your healthcare provider or pharmacist for information about FARYDAK that is written for health professionals.

What are the ingredients in FARYDAK?
Active ingredient: panobinostat
Inactive ingredients: magnesium stearate, mannitol, microcrystalline cellulose, and pre-gelatinized starch
Capsule shell contains: gelatin, FD&C Blue 1 (10 mg capsules), yellow iron oxide (10 mg and 15 mg capsules), red iron oxide (15 mg and 20 mg capsules), and titanium dioxide

Distributed by: Secura Bio, Inc., Las Vegas, NV 89134

For more information, go to www.FARYDAK.com or call 1-844-9-SECURA (1-844-973-2872).

© Secura Bio
USFPR1900101

This Medication Guide has been approved by the U.S. Food and Drug Administration.

Revised: September 2019

PACKAGE LABEL

PRINCIPAL DISPLAY PANEL

NDC 73116-100-06

6 capsules

FARYDAK®

(panobinostat)

capsules

10 mg

Equivalent to 12.58 mg of panobinostat lactate

Swallow Whole with Water and Do Not Open, Crush or Chew.

Store blister pack in original carton to protect from light.

ATTENTION: Dispense with enclosed Medication Guide

Rx only

PACKAGE LABEL

PRINCIPAL DISPLAY PANEL

NDC 73116-101-06

6 capsules

FARYDAK®

(panobinostat)

capsules

15 mg

Equivalent to 18.86 mg of panobinostat lactate

Swallow Whole with Water and Do Not Open, Crush or Chew.

Store blister pack in original carton to protect from light.

ATTENTION: Dispense with enclosed Medication Guide

Rx only

PACKAGE LABEL

PRINCIPAL DISPLAY PANEL

NDC 73116-102-06

6 capsules

FARYDAK®

(panobinostat)

capsules

20 mg

Equivalent to 25.15 mg of panobinostat lactate

Swallow Whole with Water and Do Not Open, Crush or Chew.

Store blister pack in original carton to protect from light.

ATTENTION: Dispense with enclosed Medication Guide.

Rx only